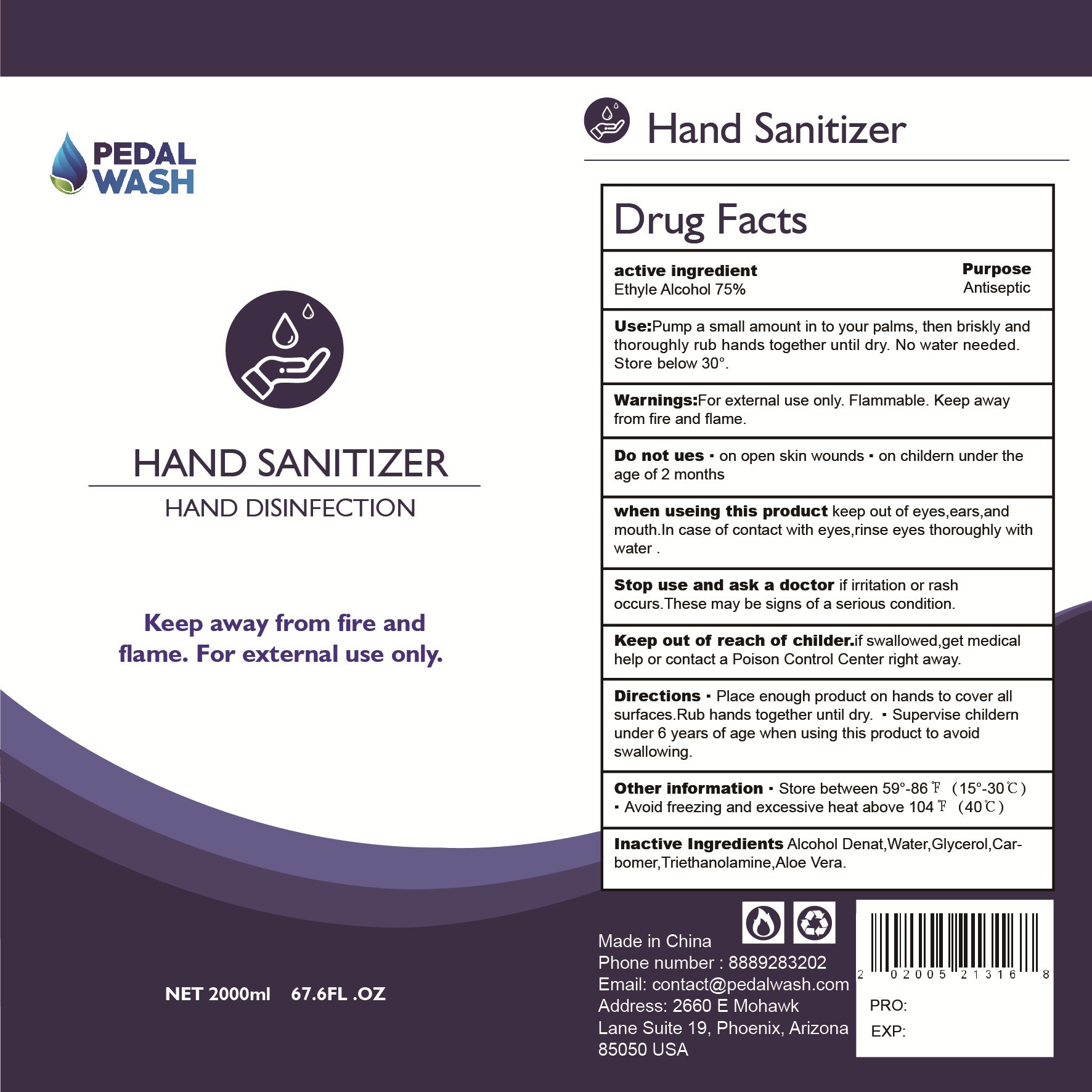 DRUG LABEL: Hand SANITIZER
NDC: 55059-002 | Form: GEL
Manufacturer: Zhe jiang OPS Environmental Technology Co.,Ltd.
Category: otc | Type: HUMAN OTC DRUG LABEL
Date: 20201215

ACTIVE INGREDIENTS: ALCOHOL 1500 mL/2000 mL
INACTIVE INGREDIENTS: ALOE; WATER; TROLAMINE; CARBOMER COPOLYMER TYPE A (ALLYL PENTAERYTHRITOL CROSSLINKED); GLYCERIN

ACTIVE INGREDIENT

Ethyle Alcohol 75%

Use

Pump a small amount in to your palms, then briskly and thoroughly rub hands together until dry.No water needed.

WARNINGS

For external use only. Flammable. Keep awayfrom fire and flame.

DO NOT USE

on open skin wounds

on childern under theage of 2 months

when using this product keep out of eyes,ears.and mouth.In case of contact with eyes,rinse eyes thoroughly withwater .

Stop use and ask a doctor if irritation or rashoccurs.These may be signs of a serious condition.

PURPOSE

Antiseptic

KEEP OUT OF REACH OF CHILDREN

Keep out of reach of childer.if swallowed,get medical help or contact a Poison Control Center right away.

Directions

Place enough product on hands to cover allsurfaces.

Rub hands together until dry.

Supervise childernunder 6 years of age when using this product to avoid.

other information

Store between 59°-86 F(15°-30℃)

Avoid freezing and excessive heat above 104 F (40°C)

INACTIVE INGREDIENT

Alcohol Denat,Water,Glycerol,Car-bomer,Triethanolamine,Aloe Vera.